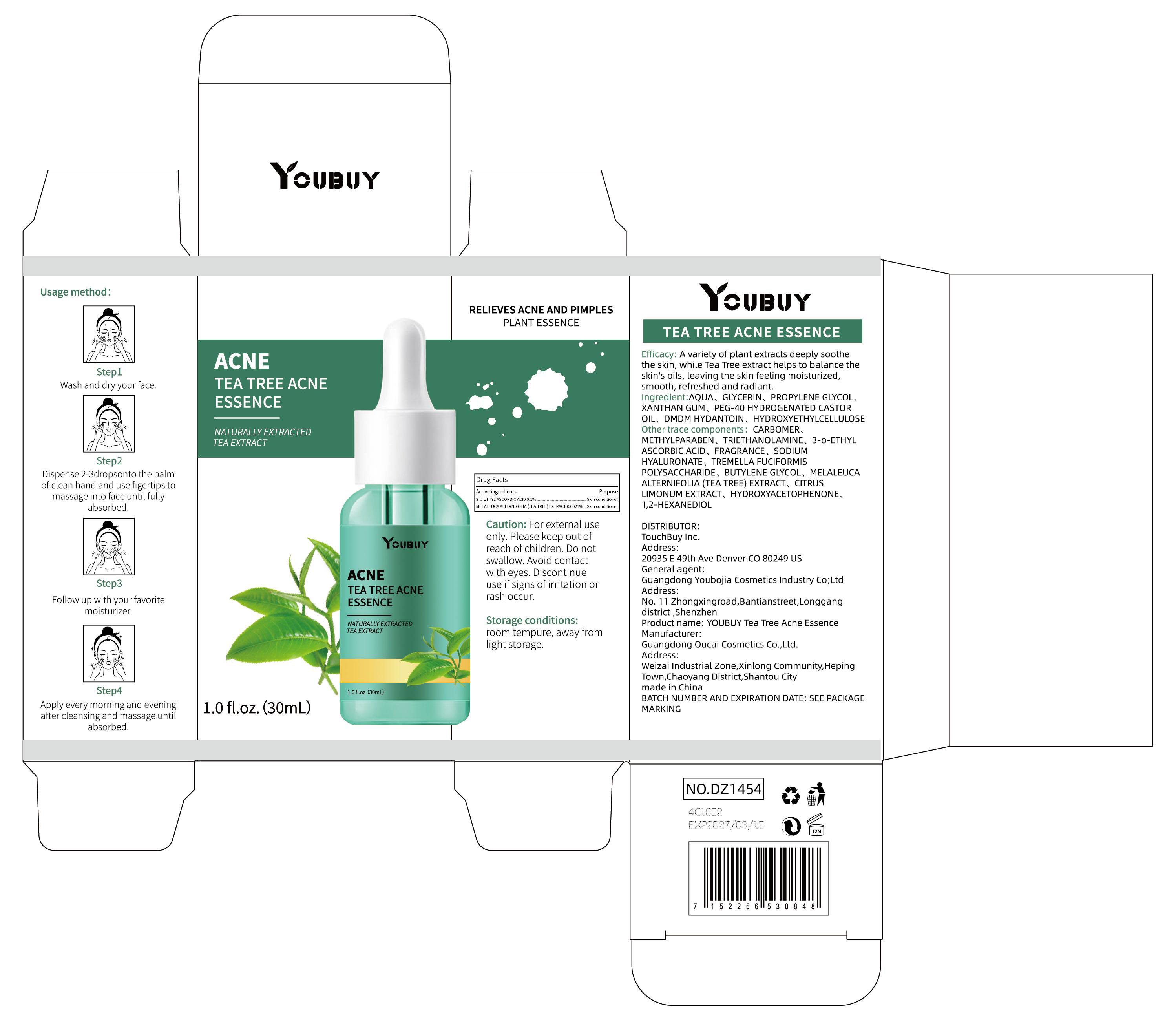 DRUG LABEL: YOUBUY TEA TREE ACNE ESSENCE
NDC: 84712-004 | Form: SOLUTION, GEL FORMING / DROPS
Manufacturer: Guangdong Youbaijia Cosmetic Industry Co., Ltd
Category: otc | Type: HUMAN OTC DRUG LABEL
Date: 20240909

ACTIVE INGREDIENTS: MELALEUCA ALTERNIFOLIA (TEA TREE) LEAF OIL 0.0007 g/30 mL; 3-O-ETHYL ASCORBIC ACID 0.03 g/30 mL
INACTIVE INGREDIENTS: GLYCERIN 1.5 g/30 mL; XANTHAN GUM 0.06 g/30 mL

ACTIVE INGREDIENT

3-o-ETHYL ASCORBIC ACID 0.1%

MELALEUCA ALTERNIFOLIA (TEA TREE) EXTRACT 0.0021%

PURPOSE

RELIEVES ACNE AND PIMPLES

INDICATIONS AND USAGE

A variety of plant extracts deeply soothethe skin, while Tea Tree extract helps to balance theskin's oils, leaving the skin feeling moisturized,smooth,refreshed and radiant.

WARNINGS

For external useonly

DO NOT USE

on damaged or broken skin

WHEN USING

Avoid contact with eyes

Discontinue use if signs ofirritation orrash occur.

KEEP OUT OF REACH OF CHILDREN

Please keep out ofreach of children. Do not swallow

room tempure, away fromlight storage.

QUESTIONS

Contact name: Jessie Peng
Company phone number: +1 818 579 7288
Company e-mail: jessie@registeragentllc.com

INACTIVE INGREDIENT

AQUA
GLYCERIN
PROPYLENE GLYCOL
XANTHAN GUM
PEG-40 HYDROGENATED CASTOR OIL
DMDM HYDANTOIN
HYDROXYETHYLCELLULOSE
CARBOMER
METHYLPARABEN
TRIETHANOLAMINE
FRAGRANCE
SODIUMHYALURONATE
TREMELLA FUCIFORMISPOLYSACCHARIDE
BUTYLENE GLYCOL
CITRUSLIMONUM EXTRACT
HYDROXYACETOPHENONE
1,2-HEXANEDIOL

DOSAGE AND ADMINISTRATION

Usage method:

- Wash and dry your face.
- Dispense 2-3dropsonto the palm of clean hand and use figertips to massage into face until fully absorbed.
- Follow up with your favorite moisturizer.
- Apply every morning and evening after cleansing and massage until absorDed.